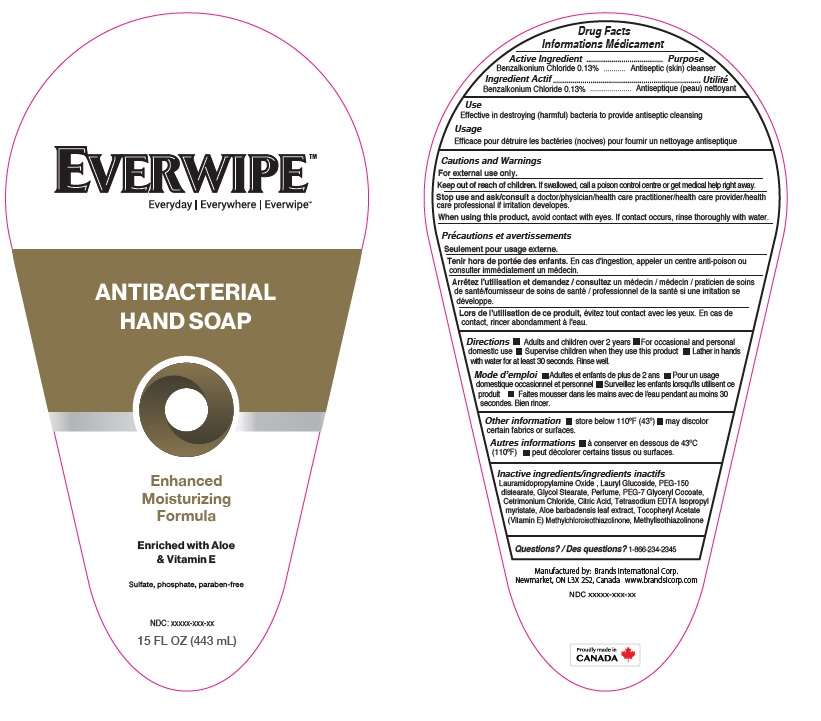 DRUG LABEL: Everwipe Antibacterial
NDC: 50157-264 | Form: LIQUID
Manufacturer: Brands International Corporation
Category: otc | Type: HUMAN OTC DRUG LABEL
Date: 20210416

ACTIVE INGREDIENTS: BENZALKONIUM CHLORIDE 1.3 mg/1 mL
INACTIVE INGREDIENTS: LAURYL GLUCOSIDE; WATER; ALOE VERA LEAF; CITRIC ACID MONOHYDRATE; CETRIMONIUM CHLORIDE; GLYCERIN; DITETRACYCLINE TETRASODIUM EDETATE; METHYLCHLOROISOTHIAZOLINONE; METHYLISOTHIAZOLINONE; .ALPHA.-TOCOPHEROL ACETATE; PEG-7 GLYCERYL COCOATE; PEG-150 DISTEARATE; GLYCOL STEARATE; LAURAMIDOPROPYLAMINE OXIDE

Everwipe Antibacterial Hand Soap

ACTIVE INGREDIENT

Benzalkonium Chloride - 0.13%

Purpose: Antibacterial

INDICATIONS AND USAGE

Effective in destroying bacteria to provide antiseptic cleaning.

DOSAGE AND ADMINISTRATION

Direction

- wet hands
- apply palmful to hands
- scrub thoroughly
- rinse

WARNINGS

For external use only

Stop use and ask a doctor if irritation or redness develops

When using this product

- do not get it into eyes. If contact occurs, rinse eye thoroughly with water

Keep out of reach of children

If swallowed, get medical help or contact a Poison Control Center right away

INACTIVE INGREDIENT

Lauramidopropylamine oxide, Lauryl glucoside, PEG-150 distearate, Glycol Stearate, Perfume, Aloe extract, Tocopheryl Acetate, Peg 7- Glyceryl Cocoate, Cetrimonium, Chloride, Citric Acid, Glycerin, Tetrasodium EDTA, Methylchloroisothiazolinone, Methylisothiazolinone.